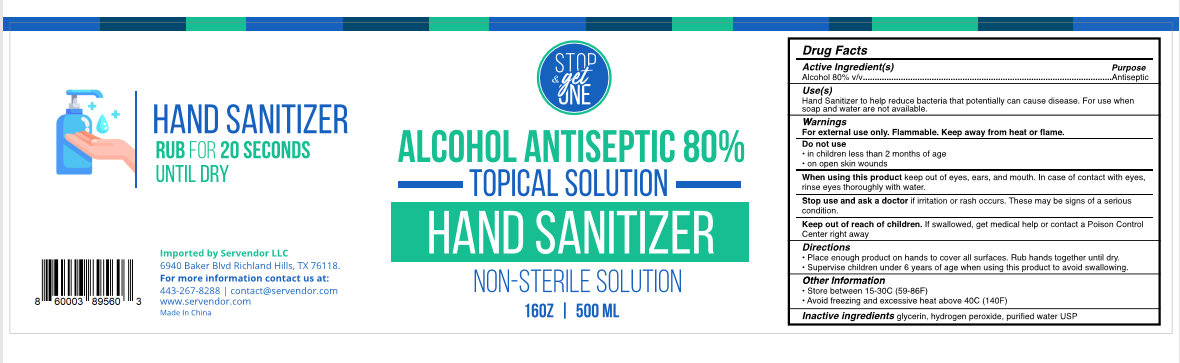 DRUG LABEL: Hand Sanitizer
NDC: 55866-004 | Form: LIQUID
Manufacturer: Guangzhou Keman Technology Co., Ltd.
Category: otc | Type: HUMAN OTC DRUG LABEL
Date: 20200514

ACTIVE INGREDIENTS: ALCOHOL 400 mL/500 mL
INACTIVE INGREDIENTS: WATER; AMMONIA; CARBOMER INTERPOLYMER TYPE A (55000 CPS)

DOSAGE AND ADMINISTRATION

Store between 15-30°C (59-86°F),Avoid freezing and excessive heat aboe 40°C (140°F).

INACTIVE INGREDIENT

Water，Acrylates/C10-30 Alkyl Acrylate Crosspolymer, Ammonium Hydroxide

INDICATIONS AND USAGE

1.Place enough product on hands to cover all surfaces. Rub hands together until dry.
2.Supervise children under 6 years of age when using this produc to avoid swallowing.

ACTIVE INGREDIENT

Ethanol

keep out of reach of children

PURPOSE

Disinfection
Sterilization

WARNINGS

For external use only. Flammable. Keep away from heat or flame.